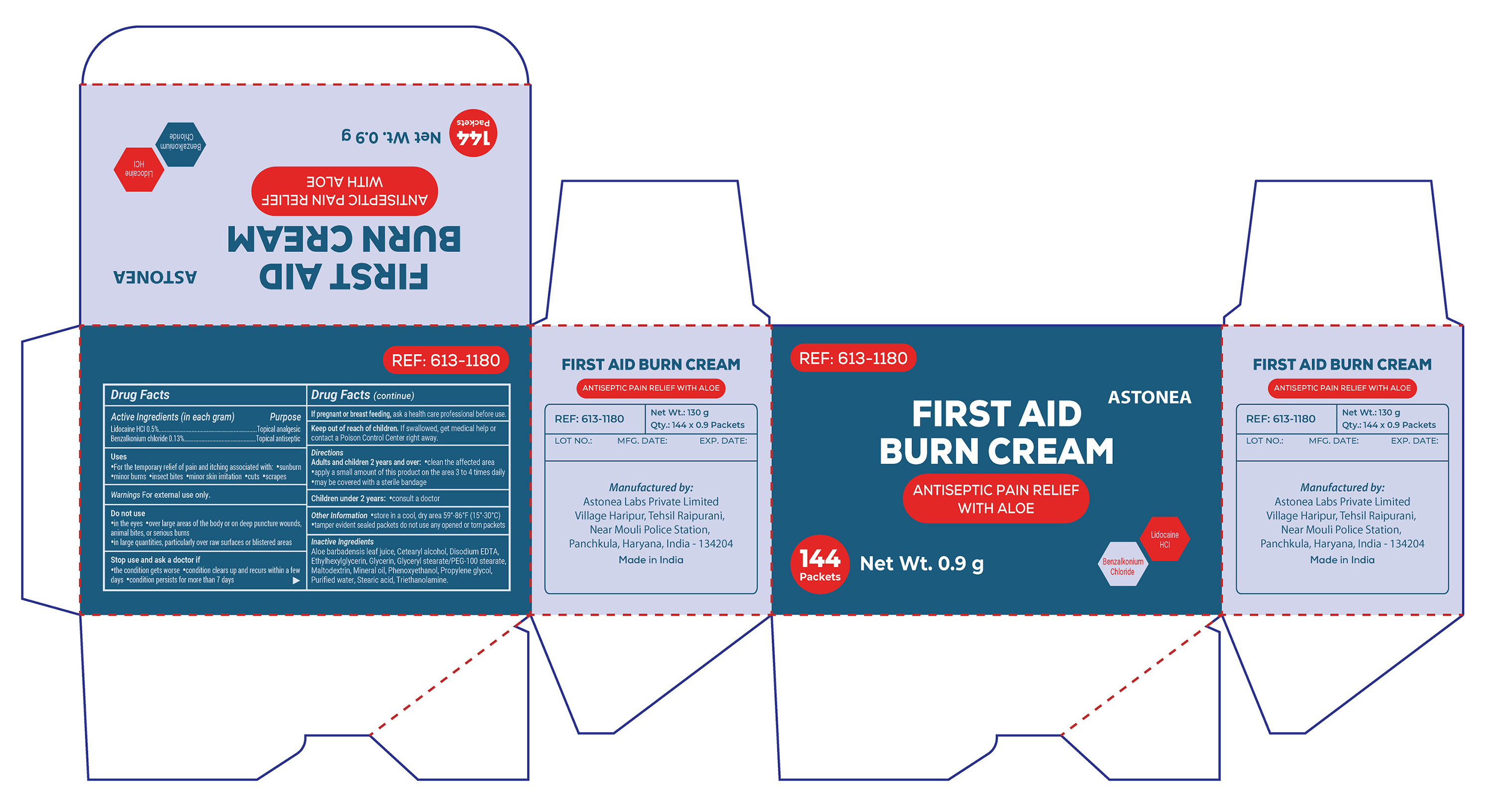 DRUG LABEL: ASTONEA Burn Cream
NDC: 77338-100 | Form: CREAM
Manufacturer: ASTONEA LABS PRIVATE LIMITED
Category: otc | Type: HUMAN OTC DRUG LABEL
Date: 20230516

ACTIVE INGREDIENTS: LIDOCAINE HYDROCHLORIDE 0.5 g/100 g; BENZALKONIUM CHLORIDE 0.13 g/100 g
INACTIVE INGREDIENTS: ALOE VERA LEAF; CETOSTEARYL ALCOHOL; EDETATE DISODIUM ANHYDROUS; ETHYLHEXYLGLYCERIN; GLYCERYL STEARATE/PEG-100 STEARATE; MALTODEXTRIN; PHENOXYETHANOL; GLYCERIN; WATER; MINERAL OIL; PROPYLENE GLYCOL; STEARIC ACID; TROLAMINE

ASTONEA Burn Cream

Active Ingredients

Lidocaine HCL 0.5% Topical Analgesic

Benzalkonium Chloride 0.13% Topical Antiseptic

Purpose

Topical Analgesic

Topical Antiseptic

Uses

For temporary relief of pain and itching associated with:

- Sunburn
- Minor burns,
- Insect bites,
- Minor skin irritation,
- Cuts
- Scrapes

Warnings

FOR EXTERNAL USE ONLY

Do Not Use

- In the eyes
- Over large areas of the body or on deep puncture wounds, animal bites or serious burns.
- In large quantities, particularly over raw surfaces or blistered areas.

Stop Use

•the condition gets worse •condition clears up and recurs within a few days •condition persists for more than 7 days

If pregnant or breast feeding

ask a health care professional before use.

KEEP OUT OF REACH OF CHILDREN

If swallowed, get medical help or contact a Poison Control Center right away.

Directions

Adults and children 2 years and over:

- clean the affected area
- apply a small amount of this product on the area 3 or 4 times daily.
- may be covered with a sterile bandage

Children under 2 years

- consult a doctor

Other Information

•store in a cool, dry area 59°-86°F (15°-30°C) •tamper evident sealed packets do not use any opened or torn packets

Inactive ingredients

Aloe barbadensis leaf juice, Cetearyl alcohol, Disodium EDTA, Ethylhexylglycerin, Glycerin, Glyceryl stearate/PEG-100 stearate, Maltodextrin, Mineral oil, Phenoxyethanol, Propylene glycol, Purified water, Stearic acid, Triethanolamine.